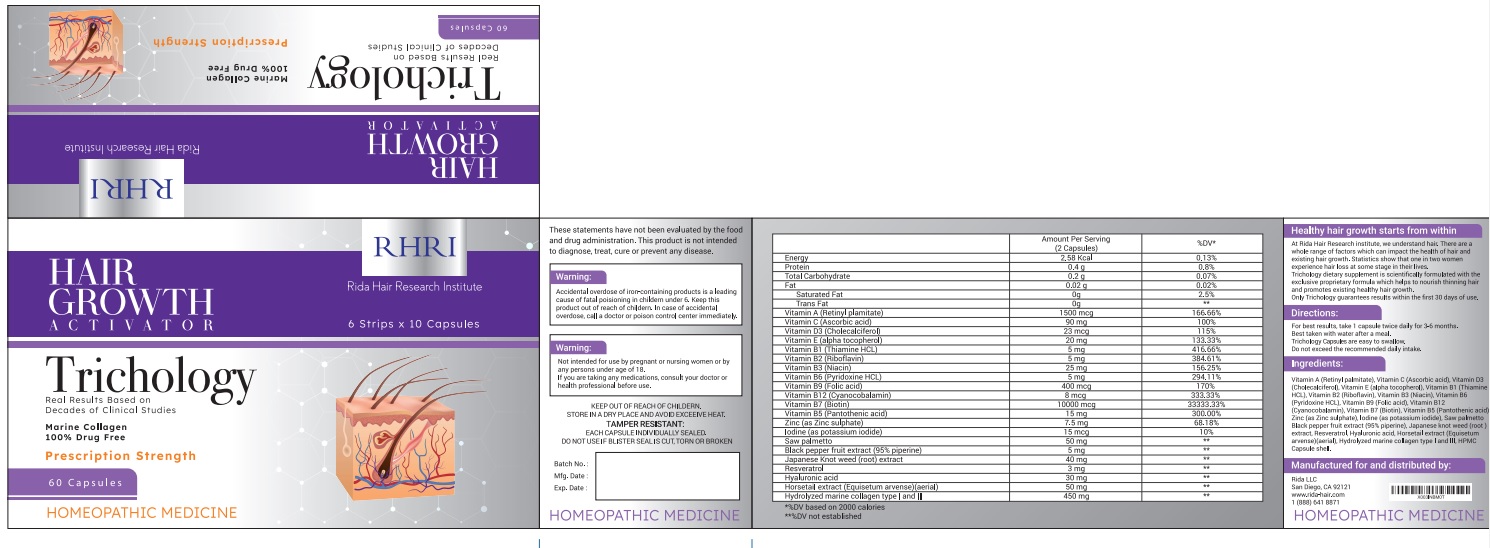 DRUG LABEL: Hair Growth
NDC: 83004-002 | Form: CAPSULE
Manufacturer: Rida LLC
Category: otc | Type: HUMAN OTC DRUG LABEL
Date: 20250307

ACTIVE INGREDIENTS: SAW PALMETTO 3 [hp_X]/1 1; BLACK PEPPER 3 [hp_X]/1 1; REYNOUTRIA JAPONICA ROOT 5 [hp_X]/1 1; EQUISETUM ARVENSE TOP 2 [hp_X]/1 1; MARINE COLLAGEN, SOLUBLE 4 [hp_X]/1 1
INACTIVE INGREDIENTS: ASCORBIC ACID; VITAMIN A PALMITATE; CHOLECALCIFEROL; .ALPHA.-TOCOPHEROL; THIAMINE HYDROCHLORIDE; RIBOFLAVIN; NIACIN; PYRIDOXINE HYDROCHLORIDE; FOLIC ACID; CYANOCOBALAMIN; BIOTIN; PANTOTHENIC ACID; ZINC SULFATE, UNSPECIFIED FORM; POTASSIUM IODIDE; RESVERATROL

Active Ingredients

Saw palmetto 3X HPUS

Black pepper fruit extract (95% piperine) 3X HPUS

Japanese Knot weed (root) extract 5X HPUS
Horsetail extract (Equisetum arvense) (aerial) 2X HPUS

Hydrolyzed marine collagen type I and III 4X HPUS

Purpose

Trichology dietary supplement is scientifically formulated with the exclusive proprietary formula which helps to nourish thinning hair and promotes existing healthy hair growth.

Uses

To nourish thinning hair and promotes existing healthy hair growth.

Warnings

Accidental overdose of iron-containing products is a leading cause of fatal poisoning in children under 6. Keep this
product out of reach of children. In case of accidental overdose, call a doctor or poison control center immediately.

Not intended for use by pregnant or nursing women or by any person under age of 18.
If you are taking any medications, consult your doctor or health professional before use.

Directions

For best results, take 1 capsule twice daily for 3-6 months.Best taken with water after a meal.
Trichology Capsules are easy to swallow. Do not exceed the recommended daily intake.

Inactive Ingredients

Vitamin A (Retinyl plamitate), Vitamin C (Ascorbic acid), Vitamin D3 (Cholecalciferol), Vitamin E (alpha tocopherol), Vitamin B1 (Thiamine HCL)
Vitamin B2 (Riboflavin), Vitamin B3 (Niacin), Vitamin B6 (Pyridoxine HCL), Vitamin B9 (Folic acid), Vitamin B12 (Cyanocobalamin), Vitamin B7 (Biotin), Vitamin B5 (Pantothenic acid), Zinc (as Zinc sulphate), lodine (as potassium iodide) Resveratrol